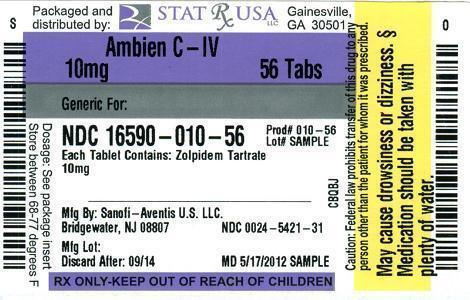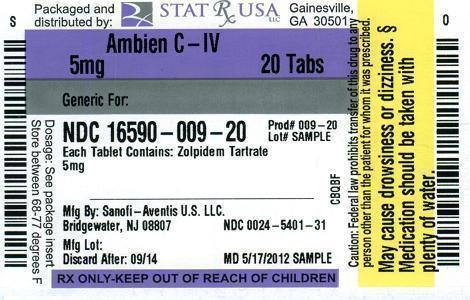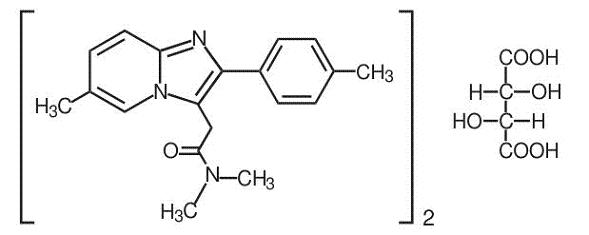 DRUG LABEL: AMBIEN
                
NDC: 16590-009 | Form: TABLET, FILM COATED
Manufacturer: STAT Rx USA LLC
Category: prescription | Type: HUMAN PRESCRIPTION DRUG LABEL
Date: 20120918
DEA Schedule: CIV

ACTIVE INGREDIENTS: ZOLPIDEM TARTRATE 5 mg/1 1
INACTIVE INGREDIENTS: HYPROMELLOSES; LACTOSE; MAGNESIUM STEARATE; CELLULOSE, MICROCRYSTALLINE; POLYETHYLENE GLYCOLS; TITANIUM DIOXIDE; FD&C RED NO. 40; POLYSORBATE 80

HIGHLIGHTS OF PRESCRIBING INFORMATION

These highlights do not include all the information needed to use AMBIEN safely and effectively. See full prescribing information for AMBIEN
Ambien® (zolpidem tartrate) tablets CIV
Initial U.S. Approval: 1992

1 INDICATIONS AND USAGE

Ambien is indicated for the short-term treatment of insomnia characterized by difficulties with sleep initiation. Ambien has been shown to decrease sleep latency for up to 35 days in controlled clinical studies. (1)

2 DOSAGE AND ADMINISTRATION

- Adult dose: 10 mg once daily immediately before bedtime (2.1)
- Elderly/debilitated patients/hepatically impaired:5 mg once daily immediately before bedtime (2.2)
- Downward dosage adjustment may be necessary when used with CNS depressants (2.3)
- Should not be taken with or immediately after a meal (2.4)

3 DOSAGE FORMS AND STRENGTHS

5 mg and 10 mg tablets. Tablets not scored (3)

4 CONTRAINDICATIONS

Known hypersensitivity to zolpidem tartrate or to any of the inactive ingredients in the formulation (4)

5 WARNINGS AND PRECAUTIONS

- Need to evaluate for co-morbid diagnosis: Reevaluate if insomnia persists after 7 to 10 days of use (5.1)
- Severe anaphylactic/anaphylactoid reactions: Angioedema and anaphylaxis have been reported. Do not rechallenge if such reactions occur. (5.2)
- Abnormal thinking, behavioral changes and complex behaviors: May include "sleep-driving" and hallucinations. Immediately evaluate any new onset behavioral changes. (5.3)
- Depression: Worsening of depression or, suicidal thinking may occur. Prescribe the least amount feasible to avoid intentional overdose (5.3, 5.6)
- Withdrawal effects: Symptoms may occur with rapid dose reduction or discontinuation. (5.4, 9.3)
- CNS depressant effects: Use can impair alertness and motor coordination. If used in combination with other CNS depressants, dose reductions may be needed due to additive effects. Do not use with alcohol (2.3, 5.5)
- Elderly/debilitated patients: Use lower dose due to impaired motor, cognitive performance and increased sensitivity (2.2, 5.6)
- Patients with hepatic impairment, mild to moderate COPD, impaired drug metabolism or hemodynamic responses, mild to moderate sleep apnea: Use with caution and monitor closely. (5.6)

6 ADVERSE REACTIONS

- Most commonly observed adverse reactions were:
  Short-term (< 10 nights): Drowsiness, dizziness, and diarrhea
  Long-term (28 – 35 nights): Dizziness and drugged feelings (6.1)

To report SUSPECTED ADVERSE REACTIONS, contact sanofi-aventis U.S. LLC at 1-800-633-1610 or FDA at 1-800-FDA-1088, or http://www.fda.gov/medwatch

7 DRUG INTERACTIONS

- CNS depressants: Enhanced CNS-depressant effects with combination use. Use with alcohol causes additive psychomotor impairment. (7.1)
- Imipramine: Decreased alertness observed with combination use. (7.1)
- Chlorpromazine: Impaired alertness and psychomotor performance observed with combination use. (7.1)
- Rifampin: Combination use decreases exposure to and effects of zolpidem. (7.2)
- Ketoconazole: Combination use increases exposure to and effect of zolpidem. (7.2)

8 USE IN SPECIFIC POPULATIONS

- Pregnancy: Based on animal data, zolpidem may cause fetal harm. (8.1)
- Nursing mothers: Zolpidem is excreted in human milk. (8.3)
- Pediatric use: Safety and effectiveness not established. Hallucinations (incidence rate 7.4%) and other psychiatric and/or nervous system adverse reactions were observed frequently in a study of pediatric patients with Attention-Deficit/Hyperactivity Disorder (5.6, 8.4)

FULL PRESCRIBING INFORMATION

1 INDICATIONS AND USAGE

Ambien (zolpidem tartrate) is indicated for the short-term treatment of insomnia characterized by difficulties with sleep initiation. Ambien has been shown to decrease sleep latency for up to 35 days in controlled clinical studies [see Clinical Studies (14)].

The clinical trials performed in support of efficacy were 4–5 weeks in duration with the final formal assessments of sleep latency performed at the end of treatment.

2 DOSAGE AND ADMINISTRATION

The dose of Ambien should be individualized.

2.1 Dosage in adults

The recommended dose for adults is 10 mg once daily immediately before bedtime. The total Ambien dose should not exceed 10 mg per day.

2.2 Special populations

Elderly or debilitated patients may be especially sensitive to the effects of zolpidem tartrate. Patients with hepatic insufficiency do not clear the drug as rapidly as normal subjects. The recommended dose of Ambien in both of these patient populations is 5 mg once daily immediately before bedtime [see Warnings and Precautions (5.6)].

2.3 Use with CNS depressants

Dosage adjustment may be necessary when Ambien is combined with other CNS depressant drugs because of the potentially additive effects [see Warnings and Precautions (5.5)].

2.4 Administration

The effect of Ambien may be slowed by ingestion with or immediately after a meal.

3 DOSAGE FORMS AND STRENGTHS

Ambien is available in 5 mg and 10 mg strength tablets for oral administration. Tablets are not scored.

Ambien 5 mg tablets are capsule-shaped, pink, film coated, with AMB 5 debossed on one side and 5401 on the other.

Ambien 10 mg tablets are capsule-shaped, white, film coated, with AMB 10 debossed on one side and 5421 on the other.

4 CONTRAINDICATIONS

Ambien is contraindicated in patients with known hypersensitivity to zolpidem tartrate or to any of the inactive ingredients in the formulation. Observed reactions include anaphylaxis and angioedema [see Warnings and Precautions (5.2)].

5 WARNINGS AND PRECAUTIONS

5.1 Need to evaluate for co-morbid diagnoses

Because sleep disturbances may be the presenting manifestation of a physical and/or psychiatric disorder, symptomatic treatment of insomnia should be initiated only after a careful evaluation of the patient. The failure of insomnia to remit after 7 to 10 days of treatment may indicate the presence of a primary psychiatric and/or medical illness that should be evaluated. Worsening of insomnia or the emergence of new thinking or behavior abnormalities may be the consequence of an unrecognized psychiatric or physical disorder. Such findings have emerged during the course of treatment with sedative/hypnotic drugs, including zolpidem.

5.2 Severe anaphylactic and anaphylactoid reactions

Rare cases of angioedema involving the tongue, glottis or larynx have been reported in patients after taking the first or subsequent doses of sedative-hypnotics, including zolpidem. Some patients have had additional symptoms such as dyspnea, throat closing or nausea and vomiting that suggest anaphylaxis. Some patients have required medical therapy in the emergency department. If angioedema involves the throat, glottis or larynx, airway obstruction may occur and be fatal. Patients who develop angioedema after treatment with zolpidem should not be rechallenged with the drug.

5.3 Abnormal thinking and behavioral changes

A variety of abnormal thinking and behavior changes have been reported to occur in association with the use of sedative/hypnotics. Some of these changes may be characterized by decreased inhibition (e.g., aggressiveness and extroversion that seemed out of character), similar to effects produced by alcohol and other CNS depressants. Visual and auditory hallucinations have been reported as well as behavioral changes such as bizarre behavior, agitation and depersonalization. In controlled trials, < 1% of adults with insomnia who received zolpidem reported hallucinations. In a clinical trial, 7.4% of pediatric patients with insomnia associated with attention-deficit/hyperactivity disorder (ADHD), who received zolpidem reported hallucinations [see Use in Specific Populations (8.4)].

Complex behaviors such as "sleep-driving" (i.e., driving while not fully awake after ingestion of a sedative-hypnotic, with amnesia for the event) have been reported with sedative-hypnotics, including zolpidem. These events can occur in sedative-hypnotic-naive as well as in sedative-hypnotic-experienced persons. Although behaviors such as "sleep-driving" may occur with Ambien alone at therapeutic doses, the use of alcohol and other CNS depressants with Ambien appears to increase the risk of such behaviors, as does the use of Ambien at doses exceeding the maximum recommended dose. Due to the risk to the patient and the community, discontinuation of Ambien should be strongly considered for patients who report a "sleep-driving" episode. Other complex behaviors (e.g., preparing and eating food, making phone calls, or having sex) have been reported in patients who are not fully awake after taking a sedative-hypnotic. As with "sleep-driving", patients usually do not remember these events. Amnesia, anxiety and other neuro-psychiatric symptoms may occur unpredictably.

In primarily depressed patients, worsening of depression, including suicidal thoughts and actions (including completed suicides), has been reported in association with the use of sedative/hypnotics.

It can rarely be determined with certainty whether a particular instance of the abnormal behaviors listed above is drug induced, spontaneous in origin, or a result of an underlying psychiatric or physical disorder. Nonetheless, the emergence of any new behavioral sign or symptom of concern requires careful and immediate evaluation.

5.4 Withdrawal effects

Following the rapid dose decrease or abrupt discontinuation of sedative/hypnotics, there have been reports of signs and symptoms similar to those associated with withdrawal from other CNS-depressant drugs [see Drug Abuse and Dependence (9)].

5.5 CNS depressant effects

Ambien, like other sedative/hypnotic drugs, has CNS-depressant effects. Due to the rapid onset of action, Ambien should only be taken immediately prior to going to bed. Patients should be cautioned against engaging in hazardous occupations requiring complete mental alertness or motor coordination such as operating machinery or driving a motor vehicle after ingesting the drug, including potential impairment of the performance of such activities that may occur the day following ingestion of Ambien. Ambien showed additive effects when combined with alcohol and should not be taken with alcohol. Patients should also be cautioned about possible combined effects with other CNS-depressant drugs. Dosage adjustments may be necessary when Ambien is administered with such agents because of the potentially additive effects.

5.6 Special populations

Use in the elderly and/or debilitated patients: Impaired motor and/or cognitive performance after repeated exposure or unusual sensitivity to sedative/hypnotic drugs is a concern in the treatment of elderly and/or debilitated patients. Therefore, the recommended Ambien dosage is 5 mg in such patients to decrease the possibility of side effects [see Dosage and Administration (2.2)]. These patients should be closely monitored.

Use in patients with concomitant illness: Clinical experience with Ambien (zolpidem tartrate) in patients with concomitant systemic illness is limited. Caution is advisable in using Ambien in patients with diseases or conditions that could affect metabolism or hemodynamic responses.

Although studies did not reveal respiratory depressant effects at hypnotic doses of zolpidem in normal subjects or in patients with mild to moderate chronic obstructive pulmonary disease (COPD), a reduction in the Total Arousal Index together with a reduction in lowest oxygen saturation and increase in the times of oxygen desaturation below 80% and 90% was observed in patients with mild-to-moderate sleep apnea when treated with Ambien (10 mg) when compared to placebo. Since sedative/hypnotics have the capacity to depress respiratory drive, precautions should be taken if Ambien is prescribed to patients with compromised respiratory function. Post-marketing reports of respiratory insufficiency, most of which involved patients with pre-existing respiratory impairment, have been received. Ambien should be used with caution in patients with sleep apnea syndrome or myasthenia gravis.

Data in end-stage renal failure patients repeatedly treated with Ambien did not demonstrate drug accumulation or alterations in pharmacokinetic parameters. No dosage adjustment in renally impaired patients is required; however, these patients should be closely monitored [see Clinical Pharmacology (12.3)].

A study in subjects with hepatic impairment did reveal prolonged elimination in this group; therefore, treatment should be initiated with 5 mg in patients with hepatic compromise, and they should be closely monitored [see Dosage and Administration (2.2) and Clinical Pharmacology (12.3)].

Use in patients with depression: As with other sedative/hypnotic drugs, Ambien should be administered with caution to patients exhibiting signs or symptoms of depression. Suicidal tendencies may be present in such patients and protective measures may be required. Intentional over-dosage is more common in this group of patients; therefore, the least amount of drug that is feasible should be prescribed for the patient at any one time.

Use in pediatric patients: Safety and effectiveness of zolpidem have not been established in pediatric patients. In an 8-week study in pediatric patients (aged 6–17 years) with insomnia associated with ADHD, zolpidem did not decrease sleep latency compared to placebo. Hallucinations were reported in 7.4% of the pediatric patients who received zolpidem; none of the pediatric patients who received placebo reported hallucinations [see Use in Specific Populations (8.4)].

6 ADVERSE REACTIONS

The following serious adverse reactions are discussed in greater detail in other sections of the labeling:

- Serious anaphylactic and anaphylactoid reactions [see Warnings and Precautions (5.2)]
- Abnormal thinking, behavior changes, and complex behaviors [see Warnings and Precautions (5.3)]
- Withdrawal effects [see Warnings and Precautions (5.4)]
- CNS-depressant effects [see Warnings and Precautions (5.5)]

6.1 Clinical trials experience

Associated with discontinuation of treatment: Approximately 4% of 1,701 patients who received zolpidem at all doses (1.25 to 90 mg) in U.S. premarketing clinical trials discontinued treatment because of an adverse reaction. Reactions most commonly associated with discontinuation from U.S. trials were daytime drowsiness (0.5%), dizziness (0.4%), headache (0.5%), nausea (0.6%), and vomiting (0.5%).

Approximately 4% of 1,959 patients who received zolpidem at all doses (1 to 50 mg) in similar foreign trials discontinued treatment because of an adverse reaction. Reactions most commonly associated with discontinuation from these trials were daytime drowsiness (1.1%), dizziness/vertigo (0.8%), amnesia (0.5%), nausea (0.5%), headache (0.4%), and falls (0.4%).

Data from a clinical study in which selective serotonin reuptake inhibitor (SSRI)-treated patients were given zolpidem revealed that four of the seven discontinuations during double-blind treatment with zolpidem (n=95) were associated with impaired concentration, continuing or aggravated depression, and manic reaction; one patient treated with placebo (n =97) was discontinued after an attempted suicide.

Most commonly observed adverse reactions in controlled trials: During short-term treatment (up to 10 nights) with Ambien at doses up to 10 mg, the most commonly observed adverse reactions associated with the use of zolpidem and seen at statistically significant differences from placebo-treated patients were drowsiness (reported by 2% of zolpidem patients), dizziness (1%), and diarrhea (1%). During longer-term treatment (28 to 35 nights) with zolpidem at doses up to 10 mg, the most commonly observed adverse reactions associated with the use of zolpidem and seen at statistically significant differences from placebo-treated patients were dizziness (5%) and drugged feelings (3%).

Adverse reactions observed at an incidence of ≥ 1% in controlled trials: The following tables enumerate treatment-emergent adverse reactions frequencies that were observed at an incidence equal to 1% or greater among patients with insomnia who received zolpidem tartrate and at a greater incidence than placebo in U.S. placebo-controlled trials. Events reported by investigators were classified utilizing a modified World Health Organization (WHO) dictionary of preferred terms for the purpose of establishing event frequencies. The prescriber should be aware that these figures cannot be used to predict the incidence of side effects in the course of usual medical practice, in which patient characteristics and other factors differ from those that prevailed in these clinical trials. Similarly, the cited frequencies cannot be compared with figures obtained from other clinical investigators involving related drug products and uses, since each group of drug trials is conducted under a different set of conditions. However, the cited figures provide the physician with a basis for estimating the relative contribution of drug and nondrug factors to the incidence of side effects in the population studied.

The following table was derived from results of 11 placebo-controlled short-term U.S. efficacy trials involving zolpidem in doses ranging from 1.25 to 20 mg. The table is limited to data from doses up to and including 10 mg, the highest dose recommended for use.

Incidence of Treatment-Emergent Adverse Experiences in Placebo-Controlled Clinical Trials Lasting up to 10 Nights (Percentage of patients reporting)
Body System/ Adverse Event [Reactions reported by at least 1% of patients treated with Ambien and at a greater frequency than placebo.] | Zolpidem (≤10 mg) (N=685) | Placebo (N=473)
Central and Peripheral Nervous System
Headache | 7 | 6
Drowsiness | 2 | -
Dizziness | 1 | -
Gastrointestinal System
Diarrhea | 1 | -

The following table was derived from results of three placebo-controlled long-term efficacy trials involving Ambien (zolpidem tartrate). These trials involved patients with chronic insomnia who were treated for 28 to 35 nights with zolpidem at doses of 5, 10, or 15 mg. The table is limited to data from doses up to and including 10 mg, the highest dose recommended for use. The table includes only adverse events occurring at an incidence of at least 1% for zolpidem patients.

Incidence of Treatment-Emergent Adverse Experiences in Placebo-Controlled Clinical Trials Lasting up to 35 Nights (Percentage of patients reporting)
Body System/ Adverse Event [Reactions reported by at least 1% of patients treated with Ambien and at a greater frequency than placebo.] | Zolpidem (≤10 mg) (N=152) | Placebo (N=161)
Autonomic Nervous System
Dry mouth | 3 | 1
Body as a Whole
Allergy | 4 | 1
Back Pain | 3 | 2
Influenza-like symptoms | 2 | -
Chest pain | 1 | -
Cardiovascular System
Palpitation | 2 | -
Central and Peripheral Nervous System
Drowsiness | 8 | 5
Dizziness | 5 | 1
Lethargy | 3 | 1
Drugged feeling | 3 | -
Lightheadedness | 2 | 1
Depression | 2 | 1
Abnormal dreams | 1 | -
Amnesia | 1 | -
Sleep disorder | 1 | -
Gastrointestinal System
Diarrhea | 3 | 2
Abdominal pain | 2 | 2
Constipation | 2 | 1
Respiratory System
Sinusitis | 4 | 2
Pharyngitis | 3 | 1
Skin and Appendages
Rash | 2 | 1

Dose relationship for adverse reactions: There is evidence from dose comparison trials suggesting a dose relationship for many of the adverse reactions associated with zolpidem use, particularly for certain CNS and gastrointestinal adverse events.

Adverse event incidence across the entire preapproval database: Ambien was administered to 3,660 subjects in clinical trials throughout the U.S., Canada, and Europe. Treatment-emergent adverse events associated with clinical trial participation were recorded by clinical investigators using terminology of their own choosing. To provide a meaningful estimate of the proportion of individuals experiencing treatment-emergent adverse events, similar types of untoward events were grouped into a smaller number of standardized event categories and classified utilizing a modified World Health Organization (WHO) dictionary of preferred terms.

The frequencies presented, therefore, represent the proportions of the 3,660 individuals exposed to zolpidem, at all doses, who experienced an event of the type cited on at least one occasion while receiving zolpidem. All reported treatment-emergent adverse events are included, except those already listed in the table above of adverse events in placebo-controlled studies, those coding terms that are so general as to be uninformative, and those events where a drug cause was remote. It is important to emphasize that, although the events reported did occur during treatment with Ambien, they were not necessarily caused by it.

Adverse events are further classified within body system categories and enumerated in order of decreasing frequency using the following definitions: frequent adverse events are defined as those occurring in greater than 1/100 subjects; infrequent adverse events are those occurring in 1/100 to 1/1,000 patients; rare events are those occurring in less than 1/1,000 patients.

Autonomic nervous system: Infrequent: increased sweating, pallor, postural hypotension, syncope. Rare: abnormal accommodation, altered saliva, flushing, glaucoma, hypotension, impotence, increased saliva, tenesmus.

Body as a whole: Frequent: asthenia. Infrequent: edema, falling, fatigue, fever, malaise, trauma. Rare: allergic reaction, allergy aggravated, anaphylactic shock, face edema, hot flashes, increased ESR, pain, restless legs, rigors, tolerance increased, weight decrease.

Cardiovascular system: Infrequent: cerebrovascular disorder, hypertension, tachycardia. Rare: angina pectoris, arrhythmia, arteritis, circulatory failure, extrasystoles, hypertension aggravated, myocardial infarction, phlebitis, pulmonary embolism, pulmonary edema, varicose veins, ventricular tachycardia.

Central and peripheral nervous system: Frequent: ataxia, confusion, euphoria, headache, insomnia, vertigo. Infrequent: agitation, anxiety, decreased cognition, detached, difficulty concentrating, dysarthria, emotional lability, hallucination, hypoesthesia, illusion, leg cramps, migraine, nervousness, paresthesia, sleeping (after daytime dosing), speech disorder, stupor, tremor. Rare: abnormal gait, abnormal thinking, aggressive reaction, apathy, appetite increased, decreased libido, delusion, dementia, depersonalization, dysphasia, feeling strange, hypokinesia, hypotonia, hysteria, intoxicated feeling, manic reaction, neuralgia, neuritis, neuropathy, neurosis, panic attacks, paresis, personality disorder, somnambulism, suicide attempts, tetany, yawning.

Gastrointestinal system: Frequent: dyspepsia, hiccup, nausea. Infrequent: anorexia, constipation, dysphagia, flatulence, gastroenteritis, vomiting. Rare: enteritis, eructation, esophagospasm, gastritis, hemorrhoids, intestinal obstruction, rectal hemorrhage, tooth caries.

Hematologic and lymphatic system: Rare: anemia, hyperhemoglobinemia, leukopenia, lymphadenopathy, macrocytic anemia, purpura, thrombosis.

Immunologic system: Infrequent: infection. Rare: abscess herpes simplex herpes zoster, otitis externa, otitis media.

Liver and biliary system: Infrequent: abnormal hepatic function, increased SGPT. Rare: bilirubinemia, increased SGOT.

Metabolic and nutritional: Infrequent: hyperglycemia, thirst. Rare: gout, hypercholesteremia, hyperlipidemia, increased alkaline phosphatase, increased BUN, periorbital edema.

Musculoskeletal system: Frequent: arthralgia, myalgia. Infrequent: arthritis. Rare: arthrosis, muscle weakness, sciatica, tendinitis.

Reproductive system: Infrequent: menstrual disorder, vaginitis. Rare: breast fibroadenosis, breast neoplasm, breast pain.

Respiratory system: Frequent: upper respiratory infection, lower respiratory infection. Infrequent: bronchitis, coughing, dyspnea, rhinitis. Rare: bronchospasm, respiratory depression, epistaxis, hypoxia, laryngitis, pneumonia.

Skin and appendages: Infrequent: pruritus. Rare: acne, bullous eruption, dermatitis, furunculosis, injection-site inflammation, photosensitivity reaction, urticaria.

Special senses: Frequent: diplopia, vision abnormal. Infrequent: eye irritation, eye pain, scleritis, taste perversion, tinnitus. Rare: conjunctivitis, corneal ulceration, lacrimation abnormal, parosmia, photopsia.

Urogenital system: Frequent: urinary tract infection. Infrequent: cystitis, urinary incontinence. Rare: acute renal failure, dysuria, micturition frequency, nocturia, polyuria, pyelonephritis, renal pain, urinary retention.

7 DRUG INTERACTIONS

7.1 CNS-active drugs

Since the systematic evaluations of zolpidem in combination with other CNS-active drugs have been limited, careful consideration should be given to the pharmacology of any CNS-active drug to be used with zolpidem. Any drug with CNS-depressant effects could potentially enhance the CNS-depressant effects of zolpidem.

Ambien was evaluated in healthy subjects in single-dose interaction studies for several CNS drugs. Imipramine in combination with zolpidem produced no pharmacokinetic interaction other than a 20% decrease in peak levels of imipramine, but there was an additive effect of decreased alertness. Similarly, chlorpromazine in combination with zolpidem produced no pharmacokinetic interaction, but there was an additive effect of decreased alertness and psychomotor performance. A study involving haloperidol and zolpidem revealed no effect of haloperidol on the pharmacokinetics or pharmacodynamics of zolpidem. The lack of a drug interaction following single-dose administration does not predict a lack following chronic administration.

An additive effect on psychomotor performance between alcohol and zolpidem was demonstrated [see Warnings and Precautions (5.5)].

A single-dose interaction study with zolpidem 10 mg and fluoxetine 20 mg at steady-state levels in male volunteers did not demonstrate any clinically significant pharmacokinetic or pharmacodynamic interactions. When multiple doses of zolpidem and fluoxetine at steady-state concentrations were evaluated in healthy females, the only significant change was a 17% increase in the zolpidem half-life. There was no evidence of an additive effect in psychomotor performance.

Following five consecutive nightly doses of zolpidem 10 mg in the presence of sertraline 50 mg (17 consecutive daily doses, at 7:00 am, in healthy female volunteers), zolpidem Cmax was significantly higher (43%) and Tmax was significantly decreased (53%). Pharmacokinetics of sertraline and N-desmethylsertraline were unaffected by zolpidem.

7.2 Drugs that affect drug metabolism via cytochrome P450

Some compounds known to inhibit CYP3A may increase exposure to zolpidem. The effect of inhibitors of other P450 enzymes has not been carefully evaluated.

A randomized, double-blind, crossover interaction study in ten healthy volunteers between itraconazole (200 mg once daily for 4 days) and a single dose of zolpidem (10 mg) given 5 hours after the last dose of itraconazole resulted in a 34% increase in AUC0–∞ of zolpidem. There were no significant pharmacodynamic effects of zolpidem on subjective drowsiness, postural sway, or psychomotor performance.

A randomized, placebo-controlled, crossover interaction study in eight healthy female subjects between five consecutive daily doses of rifampin (600 mg) and a single dose of zolpidem (20 mg) given 17 hours after the last dose of rifampin showed significant reductions of the AUC (–73%), Cmax (–58%), and T1/2 (–36%) of zolpidem together with significant reductions in the pharmacodynamic effects of zolpidem.

A randomized double-blind crossover interaction study in twelve healthy subjects showed that co-administration of a single 5 mg dose of zolpidem tartrate with ketoconazole, a potent CYP3A4 inhibitor, given as 200 mg twice daily for 2 days increased Cmax of zolpidem by a factor of 1.3 and increased the total AUC of zolpidem by a factor of 1.7 compared to zolpidem alone and prolonged the elimination half-life by approximately 30% along with an increase in the pharmacodynamic effects of zolpidem. Caution should be used when ketoconazole is given with zolpidem and consideration should be given to using a lower dose of zolpidem when ketoconazole and zolpidem are given together. Patients should be advised that use of Ambien with ketoconazole may enhance the sedative effects.

7.3 Other drugs with no interaction with zolpidem

A study involving cimetidine/zolpidem and ranitidine/zolpidem combinations revealed no effect of either drug on the pharmacokinetics or pharmacodynamics of zolpidem.

Zolpidem had no effect on digoxin pharmacokinetics and did not affect prothrombin time when given with warfarin in normal subjects.

7.4 Drug-laboratory test interactions

Zolpidem is not known to interfere with commonly employed clinical laboratory tests. In addition, clinical data indicate that zolpidem does not cross-react with benzodiazepines, opiates, barbiturates, cocaine, cannabinoids, or amphetamines in two standard urine drug screens.

8 USE IN SPECIFIC POPULATIONS

8.1 Pregnancy

TERATOGENIC EFFECTS

Pregnancy Category C

There are no adequate and well-controlled studies of Ambien in pregnant women. Ambien should be used during pregnancy only if the potential benefit justifies the potential risk to the fetus.

Administration of zolpidem to pregnant rats and rabbits resulted in adverse effects on offspring development at doses greater than the Ambien maximum recommended human dose (MRHD) of 10 mg/day (approximately 8 mg/day zolpidem base); however, teratogenicity was not observed.

When zolpidem was administered at oral doses of 4, 20, and 100 mg base/kg (approximately 5, 24 and 120 times the MRHD on a mg/m^2 basis) to pregnant rats during the period of organogenesis, dose-related decreases in fetal skull ossification occurred at all but the lowest dose, which is approximately 5 times the MRHD on a mg/m^2 basis. In rabbits treated during organogenesis with zolpidem at oral doses of 1, 4, and 16 mg base/kg (approximately 2.5, 10 and 40 times the MRHD on a mg/m^2 basis), increased embryo-fetal death and incomplete fetal skeletal ossification occurred at the highest dose. The no-effect dose for embryo-fetal toxicity in rabbits is approximately 10 times the MRHD on a mg/m^2 basis. Administration of zolpidem to rats at oral doses of 4, 20, and 100 mg base/kg (approximately 5, 24 and 120 times the MRHD on a mg/m^2 basis) during the latter part of pregnancy and throughout lactation produced decreased offspring growth and survival at all but the lowest dose, which is approximately 5 times the MRHD on a mg/m^2 basis.

Neonatal Complications

Studies in children to assess the effects of prenatal exposure to zolpidem have not been conducted; however, cases of severe neonatal respiratory depression have been reported when zolpidem was used at the end of pregnancy, especially when taken with other CNS depressants.

Children born to mothers taking sedative-hypnotic drugs may be at some risk for withdrawal symptoms during the postnatal period. Neonatal flaccidity has also been reported in infants born to mothers who received sedative-hypnotic drugs during pregnancy.

8.2 Labor and delivery

Ambien has no established use in labor and delivery [see Pregnancy (8.1)].

8.3 Nursing mothers

Zolpidem is excreted in human milk. Studies in lactating mothers indicate that the half-life of zolpidem is similar to that in non-lactating women (2.6 ± 0.3 hr). The effect of zolpidem on the nursing infant is not known. Caution should be exercised when Ambien is administered to a nursing woman.

8.4 Pediatric use

Safety and effectiveness of zolpidem have not been established in pediatric patients.

In an 8-week controlled study, 201 pediatric patients (aged 6–17 years) with insomnia associated with attention-deficit/hyperactivity disorder (90% of the patients were using psychoanaleptics) were treated with an oral solution of zolpidem (n=136), or placebo (n=65). Zolpidem did not significantly decrease latency to persistent sleep, compared to placebo, as measured by polysomnography after 4 weeks of treatment. Psychiatric and nervous system disorders comprised the most frequent (> 5%) treatment emergent adverse reactions observed with zolpidem versus placebo and included dizziness (23.5% vs. 1.5%), headache (12.5% vs. 9.2%), and hallucinations (7.4% vs. 0%) [see Warnings and Precautions(5.6)]. Ten patients on zolpidem (7.4%) discontinued treatment due to an adverse reaction.

8.5 Geriatric use

A total of 154 patients in U.S. controlled clinical trials and 897 patients in non-U.S. clinical trials who received zolpidem were ≥ 60 years of age. For a pool of U.S. patients receiving zolpidem at doses of ≤10 mg or placebo, there were three adverse reactions occurring at an incidence of at least 3% for zolpidem and for which the zolpidem incidence was at least twice the placebo incidence (i.e., they could be considered drug related).

Adverse Event | Zolpidem | Placebo
Dizziness Drowsiness Diarrhea | 3% 5% 3% | 0% 2% 1%

A total of 30/1,959 (1.5%) non-U.S. patients receiving zolpidem reported falls, including 28/30 (93%) who were ≥ 70 years of age. Of these 28 patients, 23 (82%) were receiving zolpidem doses >10 mg. A total of 24/1,959 (1.2%) non-U.S. patients receiving zolpidem reported confusion, including 18/24 (75%) who were ≥ 70 years of age. Of these 18 patients, 14 (78%) were receiving zolpidem doses >10 mg.

The dose of Ambien in elderly patients is 5 mg to minimize adverse effects related to impaired motor and/or cognitive performance and unusual sensitivity to sedative/hypnotic drugs [see Warnings and Precautions (5.6)].

9 DRUG ABUSE AND DEPENDENCE

9.1 Controlled substance

Zolpidem tartrate is classified as a Schedule IV controlled substance by federal regulation.

9.2 Abuse

Abuse and addiction are separate and distinct from physical dependence and tolerance. Abuse is characterized by misuse of the drug for non-medical purposes, often in combination with other psychoactive substances. Tolerance is a state of adaptation in which exposure to a drug induces changes that result in a diminution of one or more of the drug effects over time. Tolerance may occur to both desired and undesired effects of drugs and may develop at different rates for different effects.

Addiction is a primary, chronic, neurobiological disease with genetic, psychosocial, and environmental factors influencing its development and manifestations. It is characterized by behaviors that include one or more of the following: impaired control over drug use, compulsive use, continued use despite harm, and craving. Drug addiction is a treatable disease, using a multidisciplinary approach, but relapse is common.

Studies of abuse potential in former drug abusers found that the effects of single doses of zolpidem tartrate 40 mg were similar, but not identical, to diazepam 20 mg, while zolpidem tartrate 10 mg was difficult to distinguish from placebo.

Because persons with a history of addiction to, or abuse of, drugs or alcohol are at increased risk for misuse, abuse and addiction of zolpidem, they should be monitored carefully when receiving zolpidem or any other hypnotic.

9.3 Dependence

Physical dependence is a state of adaptation that is manifested by a specific withdrawal syndrome that can be produced by abrupt cessation, rapid dose reduction, decreasing blood level of the drug, and/or administration of an antagonist.

Sedative/hypnotics have produced withdrawal signs and symptoms following abrupt discontinuation. These reported symptoms range from mild dysphoria and insomnia to a withdrawal syndrome that may include abdominal and muscle cramps, vomiting, sweating, tremors, and convulsions. The following adverse events which are considered to meet the DSM-III-R criteria for uncomplicated sedative/hypnotic withdrawal were reported during U.S. clinical trials following placebo substitution occurring within 48 hours following last zolpidem treatment: fatigue, nausea, flushing, lightheadedness, uncontrolled crying, emesis, stomach cramps, panic attack, nervousness, and abdominal discomfort. These reported adverse events occurred at an incidence of 1% or less. However, available data cannot provide a reliable estimate of the incidence, if any, of dependence during treatment at recommended doses. Post-marketing reports of abuse, dependence and withdrawal have been received.

10 OVERDOSAGE

10.1 Signs and symptoms

In postmarketing experience of overdose with zolpidem tartrate alone, or in combination with CNS-depressant agents, impairment of consciousness ranging from somnolence to coma, cardiovascular and/or respiratory compromise, and fatal outcomes have been reported.

10.2 Recommended treatment

General symptomatic and supportive measures should be used along with immediate gastric lavage where appropriate. Intravenous fluids should be administered as needed. Zolpidem's sedative hypnotic effect was shown to be reduced by flumazenil and therefore may be useful; however, flumazenil administration may contribute to the appearance of neurological symptoms (convulsions). As in all cases of drug overdose, respiration, pulse, blood pressure, and other appropriate signs should be monitored and general supportive measures employed. Hypotension and CNS depression should be monitored and treated by appropriate medical intervention. Sedating drugs should be withheld following zolpidem overdosage, even if excitation occurs. The value of dialysis in the treatment of overdosage has not been determined, although hemodialysis studies in patients with renal failure receiving therapeutic doses have demonstrated that zolpidem is not dialyzable.

As with the management of all overdosage, the possibility of multiple drug ingestion should be considered. The physician may wish to consider contacting a poison control center for up-to-date information on the management of hypnotic drug product overdosage.

11 DESCRIPTION

Ambien (zolpidem tartrate) is a non-benzodiazepine hypnotic of the imidazopyridine class and is available in 5 mg and 10 mg strength tablets for oral administration.

Chemically, zolpidem is N,N,6-trimethyl-2-p-tolylimidazo[1,2-a] pyridine-3-acetamide L-(+)-tartrate (2:1). It has the following structure:

Zolpidem tartrate is a white to off-white crystalline powder that is sparingly soluble in water, alcohol, and propylene glycol. It has a molecular weight of 764.88.

Each Ambien tablet includes the following inactive ingredients: hydroxypropyl methylcellulose, lactose, magnesium stearate, micro-crystalline cellulose, polyethylene glycol, sodium starch glycolate, and titanium dioxide. The 5 mg tablet also contains FD&C Red No. 40, iron oxide colorant, and polysorbate 80.

12 CLINICAL PHARMACOLOGY

12.1 Mechanism of action

Zolpidem, the active moiety of zolpidem tartrate, is a hypnotic agent with a chemical structure unrelated to benzodiazepines, barbiturates, or other drugs with known hypnotic properties. It interacts with a GABA-BZ receptor complex and shares some of the pharmacological properties of the benzodiazepines. In contrast to the benzodiazepines, which non-selectively bind to and activate all BZ receptor subtypes, zolpidem in vitro binds the BZ1 receptor preferentially with a high affinity ratio of the α1/α5 subunits. This selective binding of zolpidem on the BZ1 receptor is not absolute, but it may explain the relative absence of myorelaxant and anticonvulsant effects in animal studies as well as the preservation of deep sleep (stages 3 and 4) in human studies of zolpidem tartrate at hypnotic doses.

12.3 Pharmacokinetics

The pharmacokinetic profile of Ambien is characterized by rapid absorption from the gastrointestinal tract and a short elimination half-life (T1/2) in healthy subjects.

In a single-dose crossover study in 45 healthy subjects administered 5 and 10 mg zolpidem tartrate tablets, the mean peak concentrations (Cmax) were 59 (range: 29 to 113) and 121 (range: 58 to 272) ng/mL, respectively, occurring at a mean time (Tmax) of 1.6 hours for both. The mean Ambien elimination half-life was 2.6 (range: 1.4 to 4.5) and 2.5 (range: 1.4 to 3.8) hours, for the 5 and 10 mg tablets, respectively. Ambien is converted to inactive metabolites that are eliminated primarily by renal excretion. Ambien demonstrated linear kinetics in the dose range of 5 to 20 mg. Total protein binding was found to be 92.5 ± 0.1% and remained constant, independent of concentration between 40 and 790 ng/mL. Zolpidem did not accumulate in young adults following nightly dosing with 20 mg zolpidem tartrate tablets for 2 weeks.

A food-effect study in 30 healthy male subjects compared the pharmacokinetics of Ambien 10 mg when administered while fasting or 20 minutes after a meal. Results demonstrated that with food, mean AUC and Cmax were decreased by 15% and 25%, respectively, while mean Tmax was prolonged by 60% (from 1.4 to 2.2 hr). The half-life remained unchanged. These results suggest that, for faster sleep onset, Ambien should not be administered with or immediately after a meal.

Special Populations

Elderly:

In the elderly, the dose for Ambien should be 5 mg [see Warnings and Precautions (5) and Dosage and Administration (2)]. This recommendation is based on several studies in which the mean Cmax, T1/2, and AUC were significantly increased when compared to results in young adults. In one study of eight elderly subjects (> 70 years), the means for Cmax, T1/2, and AUC significantly increased by 50% (255 vs. 384 ng/mL), 32% (2.2 vs. 2.9 hr), and 64% (955 vs. 1,562 ng∙hr/mL), respectively, as compared to younger adults (20 to 40 years) following a single 20 mg oral dose. Ambien did not accumulate in elderly subjects following nightly oral dosing of 10 mg for 1 week.

Hepatic Impairment:

The pharmacokinetics of Ambien in eight patients with chronic hepatic insufficiency were compared to results in healthy subjects. Following a single 20 mg oral zolpidem tartrate dose, mean Cmax and AUC were found to be two times (250 vs. 499 ng/mL) and five times (788 vs. 4,203 ng∙hr/mL) higher, respectively, in hepatically -compromised patients. Tmax did not change. The mean half-life in cirrhotic patients of 9.9 hr (range: 4.1 to 25.8 hr) was greater than that observed in normal subjects of 2.2 hr (range: 1.6 to 2.4 hr). Dosing should be modified accordingly in patients with hepatic insufficiency [see Dosage and Administration (2.2) and Warnings and Precautions (5.6)].

Renal Impairment:

The pharmacokinetics of zolpidem tartrate were studied in 11 patients with end-stage renal failure (mean ClCr = 6.5 ± 1.5 mL/min) undergoing hemodialysis three times a week, who were dosed with zolpidem tartrate 10 mg orally each day for 14 or 21 days. No statistically significant differences were observed for Cmax, Tmax, half-life, and AUC between the first and last day of drug administration when baseline concentration adjustments were made. On day 1, Cmax was 172 ± 29 ng/mL (range: 46 to 344 ng/mL). After repeated dosing for 14 or 21 days, Cmax was 203 ± 32 ng/mL (range: 28 to 316 ng/mL). On day 1, Tmax was 1.7 ± 0.3 hr (range: 0.5 to 3.0 hr); after repeated dosing Tmax was 0.8 ± 0.2 hr (range: 0.5 to 2.0 hr). This variation is accounted for by noting that last-day serum sampling began 10 hours after the previous dose, rather than after 24 hours. This resulted in residual drug concentration and a shorter period to reach maximal serum concentration. On day 1, T1/2 was 2.4 ± 0.4 hr (range: 0.4 to 5.1 hr). After repeated dosing, T1/2 was 2.5 ± 0.4 hr (range: 0.7 to 4.2 hr). AUC was 796 ± 159 ng∙hr/mL after the first dose and 818 ± 170 ng∙hr/mL after repeated dosing. Zolpidem was not hemodialyzable. No accumulation of unchanged drug appeared after 14 or 21 days. Zolpidem pharmacokinetics were not significantly different in renally impaired patients. No dosage adjustment is necessary in patients with compromised renal function. However, as a general precaution, these patients should be closely monitored.

13 NONCLINICAL TOXICOLOGY

13.1 Carcinogenesis, mutagenesis, impairment of fertility

Carcinogenesis:

Zolpidem was administered to mice and rats for 2 years at dietary dosages of 4, 18, and 80 mg base/kg. In mice, these doses are approximately 2.5, 10, and 50 times the maximum recommended human dose (MRHD) of 10 mg/day (8 mg zolpidem base) on mg/m^2 basis. In rats, these doses are approximately 5, 20, and 100 times the MRHD on a mg/m^2 basis. No evidence of carcinogenic potential was observed in mice. In rats, renal tumors (lipoma, liposarcoma) were seen at the mid- and high doses.

Mutagenesis:

Zolpidem was negative in in vitro (bacterial reverse mutation, mouse lymphoma, and chromosomal aberration) and in vivo (mouse micronucleus) genetic toxicology assays.

Impairment of fertility:

Oral administration of zolpidem (doses of 4, 20, and 100 mg base/kg or approximately 5, 24, and 120 times the MRHD on a mg/m^2 basis) to rats prior to and during mating, and continuing in females through postpartum day 25, resulted in irregular estrus cycles and prolonged precoital intervals. The no-effect dose for these findings is approximately 24 times the MRHD on a mg/m^2 basis. There was no impairment of fertility at any dose tested.

14 CLINICAL STUDIES

14.1 Transient insomnia

Normal adults experiencing transient insomnia (n = 462) during the first night in a sleep laboratory were evaluated in a double-blind, parallel group, single-night trial comparing two doses of zolpidem (7.5 and 10 mg) and placebo. Both zolpidem doses were superior to placebo on objective (polysomnographic) measures of sleep latency, sleep duration, and number of awakenings.

Normal elderly adults (mean age 68) experiencing transient insomnia (n = 35) during the first two nights in a sleep laboratory were evaluated in a double-blind, crossover, 2-night trial comparing four doses of zolpidem (5, 10, 15 and 20 mg) and placebo. All zolpidem doses were superior to placebo on the two primary PSG parameters (sleep latency and efficiency) and all four subjective outcome measures (sleep duration, sleep latency, number of awakenings, and sleep quality).

14.2 Chronic insomnia

Zolpidem was evaluated in two controlled studies for the treatment of patients with chronic insomnia (most closely resembling primary insomnia, as defined in the APA Diagnostic and Statistical Manual of Mental Disorders, DSM-IV™). Adult outpatients with chronic insomnia (n = 75) were evaluated in a double-blind, parallel group, 5-week trial comparing two doses of zolpidem tartrate and placebo. On objective (polysomnographic) measures of sleep latency and sleep efficiency, zolpidem 10 mg was superior to placebo on sleep latency for the first 4 weeks and on sleep efficiency for weeks 2 and 4. Zolpidem was comparable to placebo on number of awakenings at both doses studied.

Adult outpatients (n=141) with chronic insomnia were also evaluated, in a double-blind, parallel group, 4-week trial comparing two doses of zolpidem and placebo. Zolpidem 10 mg was superior to placebo on a subjective measure of sleep latency for all 4 weeks, and on subjective measures of total sleep time, number of awakenings, and sleep quality for the first treatment week.

Increased wakefulness during the last third of the night as measured by polysomnography has not been observed in clinical trials with Ambien.

14.3 Studies pertinent to safety concerns for sedative/hypnotic drugs

Next-day residual effects: Next-day residual effects of Ambien were evaluated in seven studies involving normal subjects. In three studies in adults (including one study in a phase advance model of transient insomnia) and in one study in elderly subjects, a small but statistically significant decrease in performance was observed in the Digit Symbol Substitution Test (DSST) when compared to placebo. Studies of Ambien in non-elderly patients with insomnia did not detect evidence of next-day residual effects using the DSST, the Multiple Sleep Latency Test (MSLT), and patient ratings of alertness.

Rebound effects: There was no objective (polysomnographic) evidence of rebound insomnia at recommended doses seen in studies evaluating sleep on the nights following discontinuation of Ambien (zolpidem tartrate). There was subjective evidence of impaired sleep in the elderly on the first post-treatment night at doses above the recommended elderly dose of 5 mg.

Memory impairment: Controlled studies in adults utilizing objective measures of memory yielded no consistent evidence of next-day memory impairment following the administration of Ambien. However, in one study involving zolpidem doses of 10 and 20 mg, there was a significant decrease in next-morning recall of information presented to subjects during peak drug effect (90 minutes post-dose), i.e., these subjects experienced anterograde amnesia. There was also subjective evidence from adverse event data for anterograde amnesia occurring in association with the administration of Ambien, predominantly at doses above 10 mg.

Effects on sleep stages: In studies that measured the percentage of sleep time spent in each sleep stage, Ambien has generally been shown to preserve sleep stages. Sleep time spent in stages 3 and 4 (deep sleep) was found comparable to placebo with only inconsistent, minor changes in REM (paradoxical) sleep at the recommended dose.

16 HOW SUPPLIED/STORAGE AND HANDLING

Ambien 5 mg tablets are capsule-shaped, pink, film coated, with AMB 5 debossed on one side and 5401 on the other and supplied as:

Bottles of 20 - NDC # 16590-009-20
Bottles of 30 - NDC # 16590-009-30
Bottles of 60 - NDC # 16590-009-60
Bottles of 90 - NDC # 16590-009-90

Ambien 10 mg tablets are capsule-shaped, white, film coated, with AMB 10 debossed on one side and 5421 on the other and supplied as:

Bottles of 20 - NDC # 16590-010-20
Bottles of 28 - NDC # 16590-010-28
Bottles of 30 - NDC # 16590-010-30
Bottles of 56 - NDC # 16590-010-56
Relabeling and Repackaging by:
STAT Rx USA LLC
Gainesville, GA 30501

STORAGE AND HANDLING

Store at controlled room temperature 20°–25°C (68°–77°F).

17 PATIENT COUNSELING INFORMATION

Prescribers or other healthcare professionals should inform patients, their families, and their caregivers about the benefits and risks associated with treatment with sedative-hypnotics, should counsel them in its appropriate use, and should instruct them to read the accompanying Medication Guide [see Medication Guide (17.4)].

17.1 Severe anaphylactic and anaphylactoid reactions

Inform patients that severe anaphylactic and anaphylactoid reactions have occurred with zolpidem. Describe the signs/symptoms of these reactions and advise patients to seek medical attention immediately if any of them occur.

17.2 Sleep-driving and other complex behaviors

There have been reports of people getting out of bed after taking a sedative-hypnotic and driving their cars while not fully awake, often with no memory of the event. If a patient experiences such an episode, it should be reported to his or her doctor immediately, since "sleep-driving" can be dangerous. This behavior is more likely to occur when Ambien is taken with alcohol or other central nervous system depressants [see Warnings and Precautions (5.3)]. Other complex behaviors (e.g., preparing and eating food, making phone calls, or having sex) have been reported in patients who are not fully awake after taking a sedative-hypnotic. As with "sleep-driving", patients usually do not remember these events.

In addition, patients should be advised to report all concomitant medications to the prescriber. Patients should be instructed to report events such as "sleep-driving" and other complex behaviors immediately to the prescriber.

17.3 Administration instructions

Patients should be counseled to take Ambien right before they get into bed and only when they are able to stay in bed a full night (7–8 hours) before being active again. Ambien tablets should not be taken with or immediately after a meal. Advise patients NOT to take Ambien when drinking alcohol.

MEDICATION GUIDE
AMBIEN®(ām'bē-ən) Tablets C-IV
(zolpidem tartrate)

Read the Medication Guide that comes with AMBIEN before you start taking it and each time you get a refill. There may be new information. This Medication Guide does not take the place of talking to your doctor about your medical condition or treatment.

What is the most important information I should know about AMBIEN?

After taking AMBIEN, you may get up out of bed while not being fully awake and do an activity that you do not know you are doing. The next morning, you may not remember that you did anything during the night. You have a higher chance for doing these activities if you drink alcohol or take other medicines that make you sleepy with AMBIEN. Reported activities include:

- driving a car ("sleep-driving")
- making and eating food
- talking on the phone
- having sex
- sleep-walking

Call your doctor right away if you find out that you have done any of the above activities after taking AMBIEN.

Important:

1. Take AMBIEN exactly as prescribed

- Do not take more AMBIEN than prescribed.
- Take AMBIEN right before you get in bed, not sooner.

2. Do not take AMBIEN if you:

- drink alcohol
- take other medicines that can make you sleepy. Talk to your doctor about all of your medicines. Your doctor will tell you if you can take AMBIEN with your other medicines.
- cannot get a full night's sleep

What is AMBIEN?

AMBIEN is a sedative-hypnotic (sleep) medicine. AMBIEN is used in adults for the short-term treatment of a sleep problem called insomnia. Symptoms of insomnia include:

- trouble falling asleep

AMBIEN is not for children.

BOXED WARNING

AMBIEN is a federally controlled substance (C-IV) because it can be abused or lead to dependence. Keep AMBIEN in a safe place to prevent misuse and abuse. Selling or giving away AMBIEN may harm others, and is against the law. Tell your doctor if you have ever abused or have been dependent on alcohol, prescription medicines or street drugs.

Who should not take AMBIEN?

Do not take AMBIEN if you are allergic to anything in it.

See the end of this Medication Guide for a complete list of ingredients in AMBIEN.

AMBIEN may not be right for you. Before starting AMBIEN, tell your doctor about all of your health conditions, including if you:

- have a history of depression, mental illness, or suicidal thoughts
- have a history of drug or alcohol abuse or addiction
- have kidney or liver disease
- have a lung disease or breathing problems
- are pregnant, planning to become pregnant, or breastfeeding

Tell your doctor about all of the medicines you take including prescription and nonprescription medicines, vitamins and herbal supplements. Medicines can interact with each other, sometimes causing serious side effects. Do not take AMBIEN with other medicines that can make you sleepy.

Know the medicines you take. Keep a list of your medicines with you to show your doctor and pharmacist each time you get a new medicine.

How should I take AMBIEN?

- Take AMBIEN exactly as prescribed. Do not take more AMBIEN than prescribed for you.
- Take AMBIEN right before you get into bed.
- Do not take AMBIEN unless you are able to stay in bed a full night (7–8 hours) before you must be active again.
- For faster sleep onset, AMBIEN should NOT be taken with or immediately after a meal.
- Call your doctor if your insomnia worsens or is not better within 7 to 10 days. This may mean that there is another condition causing your sleep problem.
- If you take too much AMBIEN or overdose, call your doctor or poison control center right away, or get emergency treatment.

What are the possible side effects of AMBIEN?

Serious side effects of AMBIEN include:

- getting out of bed while not being fully awake and do an activity that you do not know you are doing. (See "What is the most important information I should know about AMBIEN?)
- abnormal thoughts and behavior. Symptoms include more outgoing or aggressive behavior than normal, confusion, agitation, hallucinations, worsening of depression, and suicidal thoughts or actions.
- memory loss
- anxiety
- severe allergic reactions. Symptoms include swelling of the tongue or throat, trouble breathing, and nausea and vomiting. Get emergency medical help if you get these symptoms after taking AMBIEN.

Call your doctor right away if you have any of the above side effects or any other side effects that worry you while using AMBIEN.

The most common side effects of AMBIEN are:

- drowsiness
- dizziness
- diarrhea
- "drugged feelings"
- You may still feel drowsy the next day after taking AMBIEN. Do not drive or do other dangerous activities after taking AMBIEN until you feel fully awake.

After you stop taking a sleep medicine, you may have symptoms for 1 to 2 days such as: trouble sleeping, nausea, flushing, lightheadedness, uncontrolled crying, vomiting, stomach cramps, panic attack, nervousness, and stomach area pain.

These are not all the side effects of AMBIEN. Ask your doctor or pharmacist for more information.

Call your doctor for medical advice about side effects. You may report side effects to FDA at 1–800–FDA–1088.

How should I store AMBIEN?

- Store AMBIEN at room temperature, 68° to 77°F (20° to 25°C).
- Keep AMBIEN and all medicines out of reach of children.

General Information about AMBIEN

- Medicines are sometimes prescribed for purposes other than those listed in a Medication Guide.
- Do not use AMBIEN for a condition for which it was not prescribed.
- Do not share AMBIEN with other people, even if you think they have the same symptoms that you have. It may harm them and it is against the law.

This Medication Guide summarizes the most important information about AMBIEN. If you would like more information, talk with your doctor. You can ask your doctor or pharmacist for information about AMBIEN that is written for healthcare professionals. For more information about AMBIEN, call 1-800-633-1610.

What are the ingredients in AMBIEN?

Active Ingredient: Zolpidem tartrate

Inactive Ingredients: hydroxypropyl methylcellulose, lactose, magnesium stearate, micro-crystalline cellulose, polyethylene glycol, sodium starch glycolate, and titanium dioxide. In addition, the 5 mg tablet contains FD&C Red No. 40, iron oxide colorant, and polysorbate 80.

This Medication Guide has been approved by the U.S. Food and Drug Administration.

sanofi-aventis U.S. LLC
Bridgewater, NJ 08807
A SANOFI COMPANY

May 2012

© 2012 sanofi-aventis U.S. LLC

Relabeling and Repackaging by:

STAT Rx USA LLC

Gainesville, GA 30501